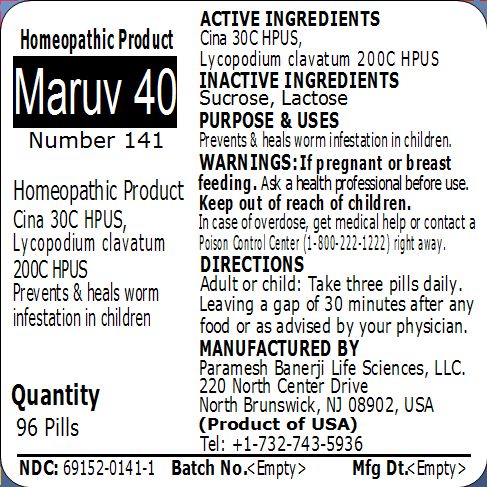 DRUG LABEL: Maruv 40 Number 141
NDC: 69152-0141 | Form: PELLET
Manufacturer: Paramesh Banerji Life Sciences LLC
Category: homeopathic | Type: HUMAN OTC DRUG LABEL
Date: 20150303

ACTIVE INGREDIENTS: LYCOPODIUM CLAVATUM SPORE 200 [hp_C]/1 1; ARTEMISIA CINA PRE-FLOWERING TOP 30 [hp_C]/1 1
INACTIVE INGREDIENTS: SUCROSE; LACTOSE

Active Ingredients

Cina 30C HPUS, Lycopodium clavatum 200C HPUS

Inactive Ingredients

Sucrose, Lactose

Purpose

Prevents & heals worm infestation in children

Uses

Prevents & heals worm infestation in children

Warnings

If pregnant or breast feeding ask a health professional before use.

Keep out of reach of children. In case of overdose, get medical help or contact a Poison Control Center (1-800-222-1222) right away.

Direction

Adult or child: Take three pills daily. Leaving a gap of 30 minutes after any food or as advised by your physician.

Manufactured by

Paramesh Banerji Life Sciences, LLC

220 North Center Drive

North Brunswick, NJ 08902, USA

Product of USA

Tel: +1-732-743-5936

Principal Display Panel

Homeopathic Product

Maruv 40

Number 141

Homeopathic Product

Cina 30C HPUS, Lycopodium clavatum 200C HPUS

Prevents & heals worm infestation in children

Quantity

96 Pills